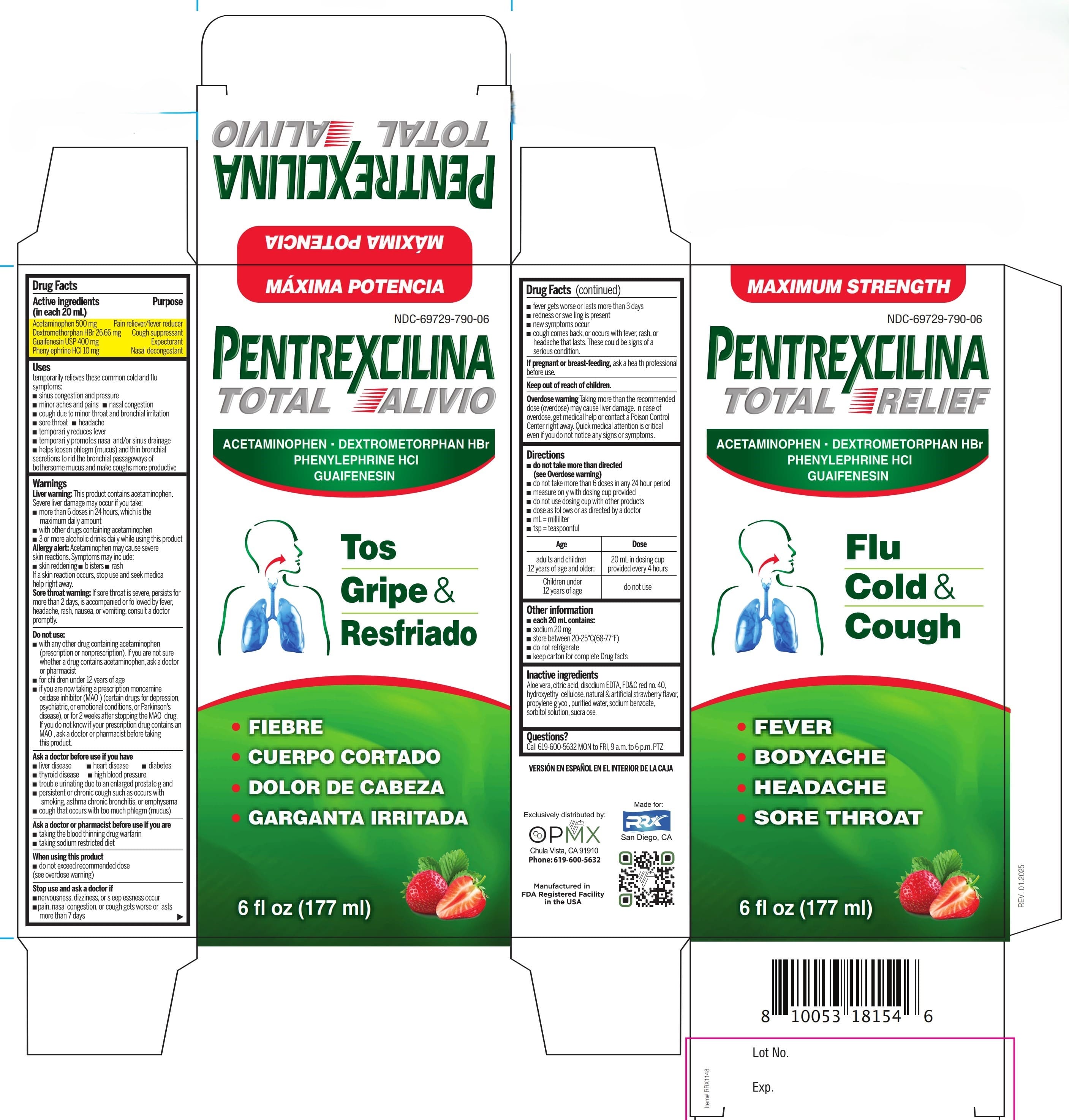 DRUG LABEL: Pentrexcilina Adult TOTAL RELIEF Multi-Symptom
NDC: 69729-790 | Form: SYRUP
Manufacturer: OPMX LLC
Category: otc | Type: HUMAN OTC DRUG LABEL
Date: 20250117

ACTIVE INGREDIENTS: PHENYLEPHRINE HYDROCHLORIDE 10 mg/20 mL; ACETAMINOPHEN 500 mg/20 mL; DEXTROMETHORPHAN HYDROBROMIDE 26.66 mg/20 mL; GUAIFENESIN 400 mg/20 mL
INACTIVE INGREDIENTS: EDETATE DISODIUM; FD&C RED NO. 40; HYDROXYETHYL CELLULOSE, UNSPECIFIED; PROPYLENE GLYCOL; ALOE VERA WHOLE; ANHYDROUS CITRIC ACID; SORBITOL SOLUTION; SUCRALOSE; WATER; SODIUM BENZOATE

Pentrexcilina Adult TOTAL RELIEF Multi-Symptom

Active ingredients

Purpose

Active ingredients (in each 10mL=2 teaspoonful) | Purpose
Acetaminophen 500 mg | Pain reliever/ fever reducer
Dextromethorphan HBr 26.66 mg | Cough suppressant
Guaifenesin 400 mg | Expectorant
Phenylephrine HCl 10 mg | Nasal decongestant

Uses

temporarily relieves these common cold and flu symptoms:

- sinus congestion and pressure
- minor aches and pains
- nasal congestion
- cough due to minor throat and bronchial irritation
- sore throat
- headache
- temporarily reduces fever
- temporarily promotes nasal and/or sinus drainage
- helps loosen phlegm (mucus) and thin bronchial secretions to rid the bronchial passageways of bothersome mucus and make coughs more productive

Warnings

Liver warning

This product contains acetaminophen.

Severe liver damage may occur if you take:

- more than 6 doses in 24 hours, which is the maximum daily amount
- with other drugs containing acetaminophen
- 3 or more alcoholic drinks daily while using this product

Allergy alert

Acetaminophen may cause severe skin reactions. Symptoms may include:

- skin reddening
- blisters
- rash

If a skin reaction occurs, stop use and seek medical help right away.

Sore throat warning

If sore throat is severe, persists for more than 2 days, is accompanied or followed by fever, headache, rash, nausea, or vomiting, consult a doctor promptly.

Do not use

- with any other drug containing acetaminophen (prescription or nonprescription). If you are not sure whether a drug contains acetaminophen, ask a doctor or pharmacist
- for children under 12 years of age
- if you are now taking a prescription monoamine oxidase inhibitor (MAOI) (certain drugs for depression, psychiatric, or emotional conditions, or Parkinson´s disease), or for 2 weeks after stopping the MAOI drug.If you do not know if your prescription drug contains an MAOI, ask a doctor or pharmacist before taking this product.

Ask a doctor before use if you have

- liver disease
- heart disease
- diabetes
- thyroid disease
- high blood pressure
- trouble urinating due to an enlarged prostate gland
- persistent or chronic cough such as occurs with smoking, asthma chronic bronchitis, or emphysema
- cough that occurs with too much phlegm (mucus)

Ask a doctor or pharmacist before use if you are

- taking the blood thinning drug warfarin
- taking sodium restricted diet

When using this product

do not exceed recommended dose (see overdose warning).

Stop use and ask a doctor if

- nervousness, dizziness, or sleeplessness occur
- pain, nasal congestion, or cough gets worse or lasts more than 7 days
- fever gets worse or lasts more than 3 days
- redness or swelling is present
- new symptoms occur
- cough comes back, or occurs with fever, rash, or headache that lasts. These could be signs of a serious condition.

If pregnant or breast-feeding

ask a health professional before use.

Keep out of reach of children

Overdose warning

Taking more than the recommended dose (overdose) may cause liver damage. In case of overdose, get medical help or contact a Poison Control Center right away. Quick medical attention is critical even if you do not notice any sings or symptms.

Directions

- do not take more than directed (see Overdose warning)
- do not take more than 6 doses in any 24 hour period
- measure only with dosing cup provided
- do not use dosing cup with other products
- dose as follows or as directed by a doctor
- mL=mililiter
- tsp=teaspoonful

Age | Dose
adults and children 12 years of age and older: | 20 mL in dosing cup provided every 4 hours
Children under 12 years of age | do not use

Other information

- each 10 mL contains:
- sodium 10mg
- store between 20-25°C (68-77°F)
- do not refrigerate
- keep carton for complete Drug Facts

Inactive ingredients

Aloe vera, citric acid, disodium EDTA, FD&C red no. 40, hydroxyethyl cellulose, natural & artificial strawberry flavor, propylene glycol USP, purified water, sodium benzoate, sorbitol solution, sucralose.

Questions?

Call 619-600-5632 MN to FRI, 9 a.m. to 6 p.m. PTZ

PACKAGE LABEL

MAXIMUM STRENGHT

NDC 69729-790-06

PENTREXCILINA

TOTAL RELIEF

ACETAMINOPHEN

DEXTROMETORPHAN HBr

PHENYLEPHRINE HCl

GUAIFENESIN

Flu

Cold &

Cough

- FEVER
- BODYACHE
- HEADACHE
- SORE THROAT

6fl oz (177ml)

VERSIÓN EN ESPAÑOL EN EL INTERIOR DE LA CAJA

Exclusively distributed by:

OPMX

Chula Vista, CA 91910

Manufactured in FDA Registered in the USA